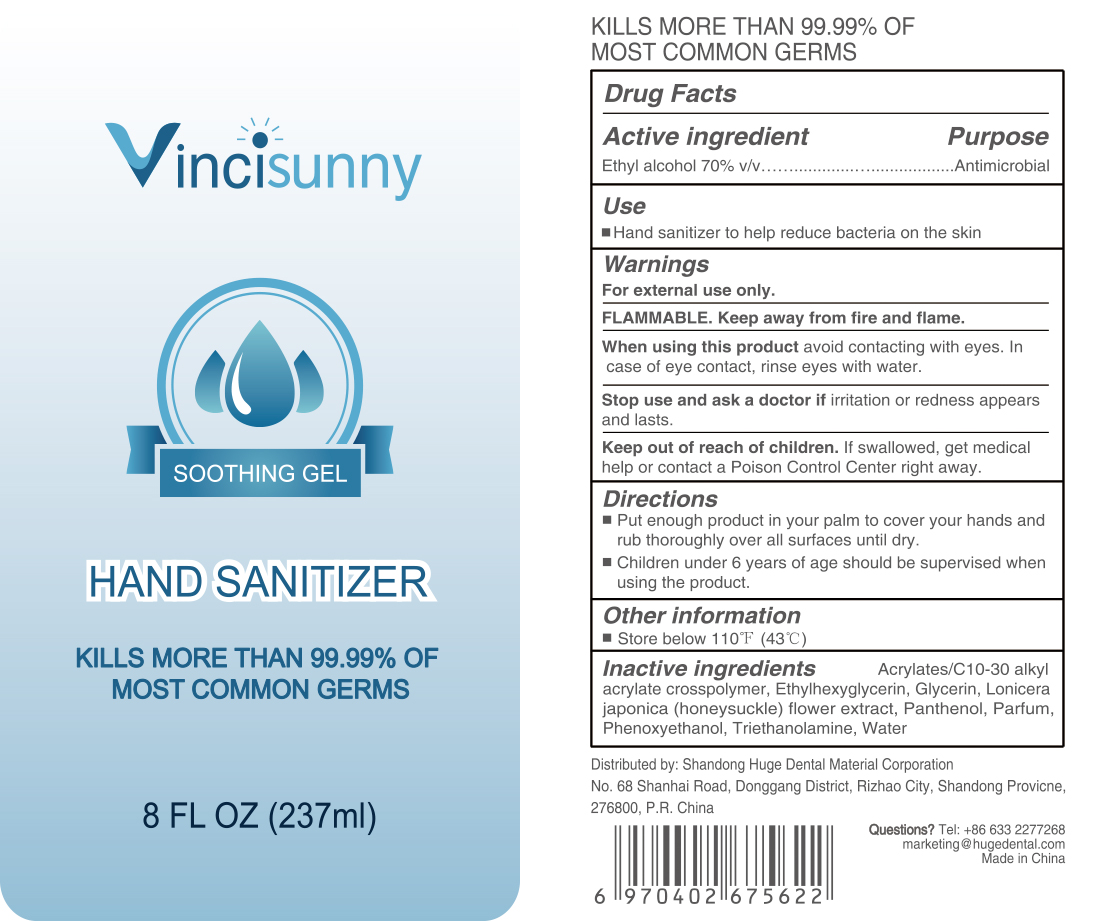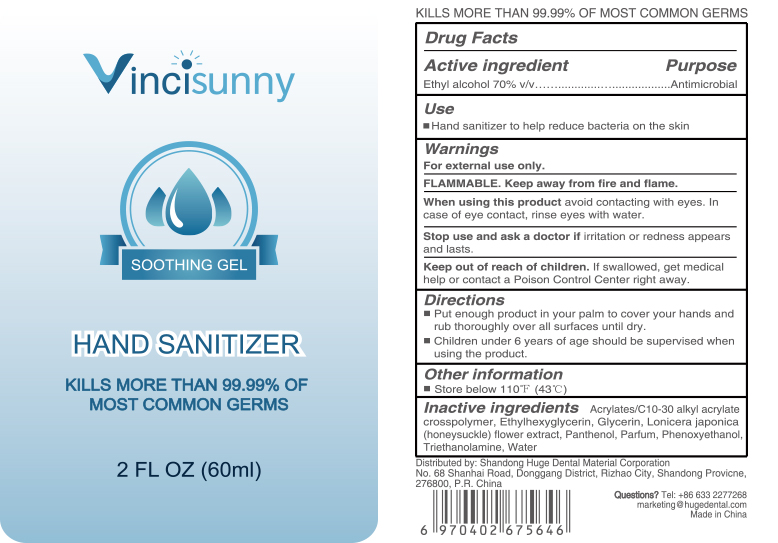 DRUG LABEL: Vincisunny Hand Sanitizer
NDC: 73718-003 | Form: GEL
Manufacturer: Shandong Huge Dental Material Corporation
Category: otc | Type: HUMAN OTC DRUG LABEL
Date: 20200417

ACTIVE INGREDIENTS: ALCOHOL 0.7 mL/1 mL
INACTIVE INGREDIENTS: WATER

Hand Sanitizer 70% (v/v) NDC

Dosage and administration section

Dosage: GEL

Administration: TOPICAL

Active ingredient

Ethyl alcohol 70% v/v

Inactive ingredients

Acrylates/C10-30 alkyl acrylate crosspolymer, Ethylhexyglycerin, Glycerin, Lonicera japonica (honeysuckle) flower extract, Panthenol, Parfum, Phenoxyethanol, Triethanolamine, Water

Indications and usage

Indications & usage: Hand sanitizer to help reduce bacteria on the skin

Purpose

Purpose: Antimicrobial

Warnings

For external use only.

FLAMMABLE. Keep away from fire and flame.

When using this product avoid contacting with eyes. In case of eye contact, rinse eyes with water.

Stop use and ask a doctor if irritation or redness appears and lasts.

Keep out of reach of children. If swallowed, get medical help or contact a Poison Control Center right away.